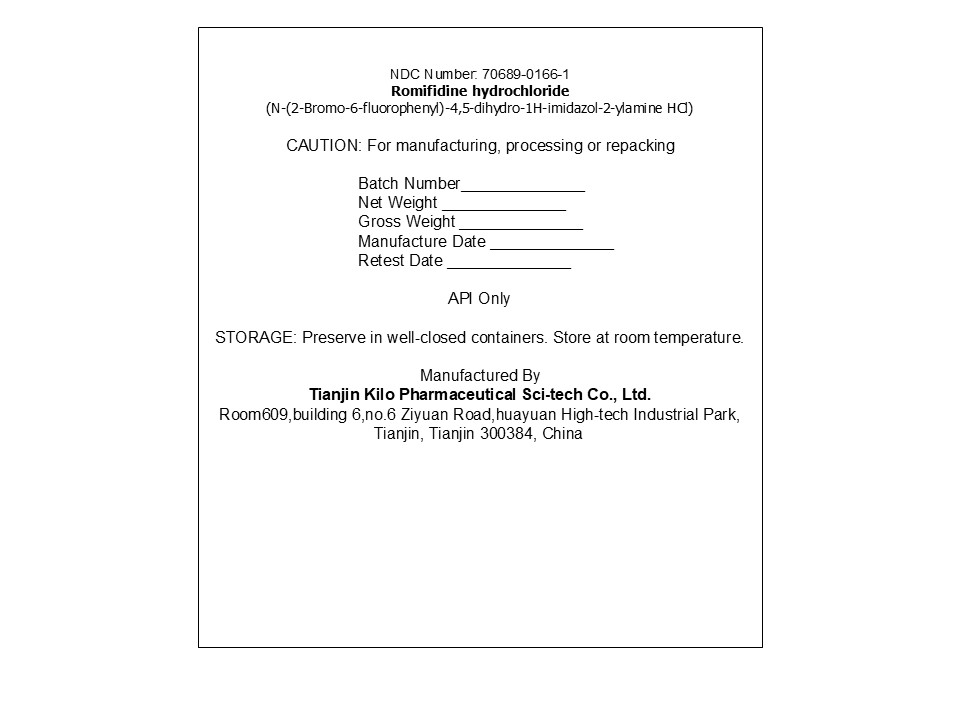 DRUG LABEL: Romifidine hydrochloride
NDC: 70689-0166 | Form: POWDER
Manufacturer: Tianjin Kilo Pharmaceutical Scitech Co Ltd
Category: other | Type: BULK INGREDIENT - ANIMAL DRUG
Date: 20251217

ACTIVE INGREDIENTS: Romifidine hydrochloride 50 g/50 g

PACKAGE LABEL

NDC Number: 70689-0166-1
Romifidine hydrochloride
(N-(2-Bromo-6-fluorophenyl)-4,5-dihydro-1H-imidazol-2-ylamine HCl)

CAUTION: For manufacturing, processing or repacking

Batch Number______________
Net Weight ______________
Gross Weight ______________
Manufacture Date ______________
Retest Date ______________

API Only

STORAGE: Preserve in well-closed containers. Store at room temperature.

Manufactured By
Tianjin Kilo Pharmaceutical Sci-tech Co., Ltd.
Room609,building 6,no.6 Ziyuan Road,huayuan High-tech Industrial Park, Tianjin, Tianjin 300384, China